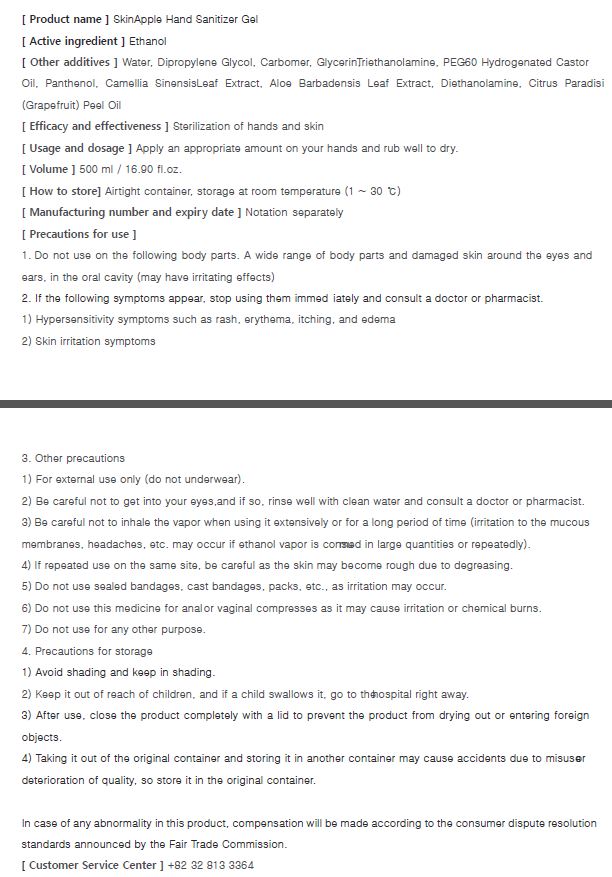 DRUG LABEL: SKINAPPLE HAND SANITIZER gel
NDC: 74247-0003 | Form: GEL
Manufacturer: Rainbow Co Ltd
Category: otc | Type: HUMAN OTC DRUG LABEL
Date: 20200408

ACTIVE INGREDIENTS: ALCOHOL 70 g/100 mL
INACTIVE INGREDIENTS: TROLAMINE; GLYCERIN; WATER; CARBOMER 940

Drug Facts

ACTIVE INGREDIENT

ethyl alcohol

INACTIVE INGREDIENT

Water, Glycerin, Carbomer, dipropylene glycol, triethaneolamine, peg-60 hydrogenated castor oil, panthenol, camellia sinensis leaf extract, diethanolamine, grapefruit peel oil

PURPOSE

to desrease bacteria on hands.

KEEP OUT OF REACH OF THE CHILDREN

INDICATIONS AND USAGE

Apply to clean, dry hands. Apply sufficient amount to thoroughly wet all surfaces of hands and fingers. Rub onto hands until dry.

Supervise children in the use of this product.

WARNINGS

■ Flammable. Keep away from fire or flame.

■ For external use only.

■ Do not use in eyes.

■ lf swallowed, get medical help promptly.

■ Stop use, ask doctor lf irritation occurs.

■ Keep out of reach of children.

DOSAGE AND ADMINISTRATION

for external use only